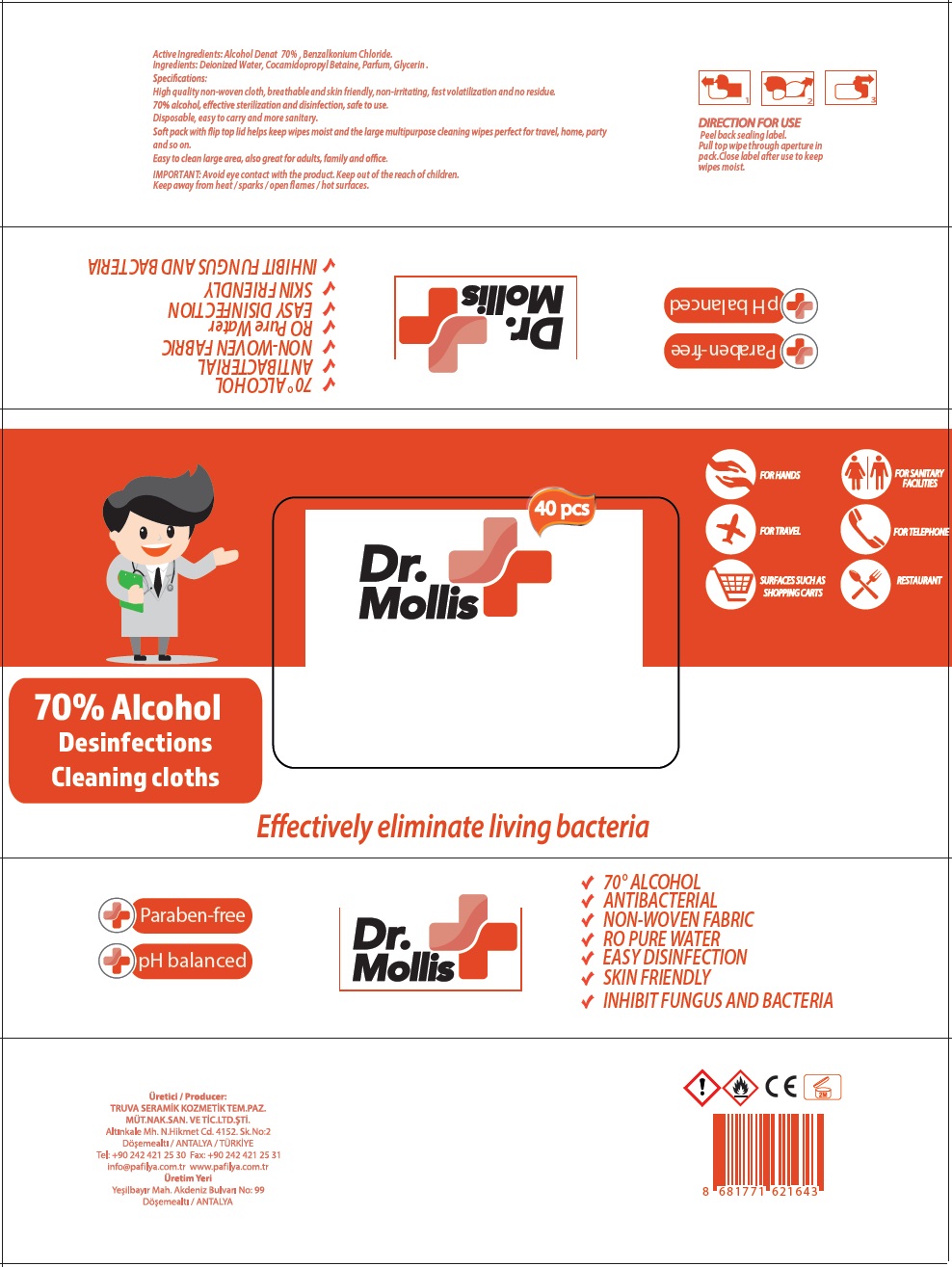 DRUG LABEL: Dr.Mollis Alcohol Wet Wipes
NDC: 79259-010 | Form: CLOTH
Manufacturer: TRUVA SERAMIK KOZMETIK TEMIZLIK PAZARLAMA MUTEAHHITLIK NAKLIYAT SANAYI VE TICARET LTD STI
Category: otc | Type: HUMAN OTC DRUG LABEL
Date: 20200703

ACTIVE INGREDIENTS: ALCOHOL 70 mL/100 mL; BENZALKONIUM CHLORIDE 0.1 g/100 mL
INACTIVE INGREDIENTS: WATER; COCAMIDOPROPYL BETAINE; GLYCERIN

Dr. Mollis 70% Alcohol Disinfections Cleaning Cloths

ACTIVE INGREDIENT

Active Ingredients: Alcohol Denat 70% , Benzalkonium Chloride 0.1%

Purpose: Antibacterial

INDICATIONS AND USAGE

Use: Decreases bacteria on the skin

WARNINGS

IMPORTANT: Avoid eye contact with the product.

Keep away from heat / sparks / open flames / hot surfaces.

Keep out of the reach of children.

DIRECTION FOR USE

Peel back sealing label.

Pull top wipe through aperture in pack.Close label after use to keep wipes moist.

INACTIVE INGREDIENT

Inactive Ingredients: Deionized Water, Cocamidopropyl Betaine, Parfum, Glycerin.

Effectively eliminate living bacteria

FOR HANDS

FOR TRAVEL

SURFACES SUCH AS SHOPPING CARTS

FOR SANITARY FACILITIES

FOR TELEPHONE

RESTAURANT

+ Paraben-free

+ pH balanced

- 70° ALCOHOL
- ANTIBACTERIAL
- NON-WOVEN FABRIC
- RO PURE WATER
- EASY DISINFECTION
- SKIN FRIENDLY
- INHIBIT FUNGUS AND BACTERIA

Specifications:

High quality non-woven cloth, breathable and skin friendly, non-irritating, fast volatilization and no residue.

70% alcohol, effective sterilization and disinfection, safe to use

Disposable, easy to carry and more sanitary.

Soft pack with flip top lid helps keep wipes moist and large multipurpose cleaning wipes perfect for travel, home, party and so on.

Easy to clean large area, also great for adults, family and office.

Üretici / Producer:

TRUVA SERAMIK KOZMETIK TEM. PAZ.

MÜT.NAK.SAN.TIC.LTD.ŞTI.

Altınkale Mh. N. Hikmet Cd. 4152. Sk. No:2

Döşemealti / ANTALYA / TÜRKİYE

Tel: +90 242 421 25 30 Fax: +90 242 421 25 31

info@pafilya.com.tr www.pafilya.com.tr

Üretim Yeri

yeşilbayir Mah. Akdeniz Bulvari No: 99

Döşemealti / ANTALYA